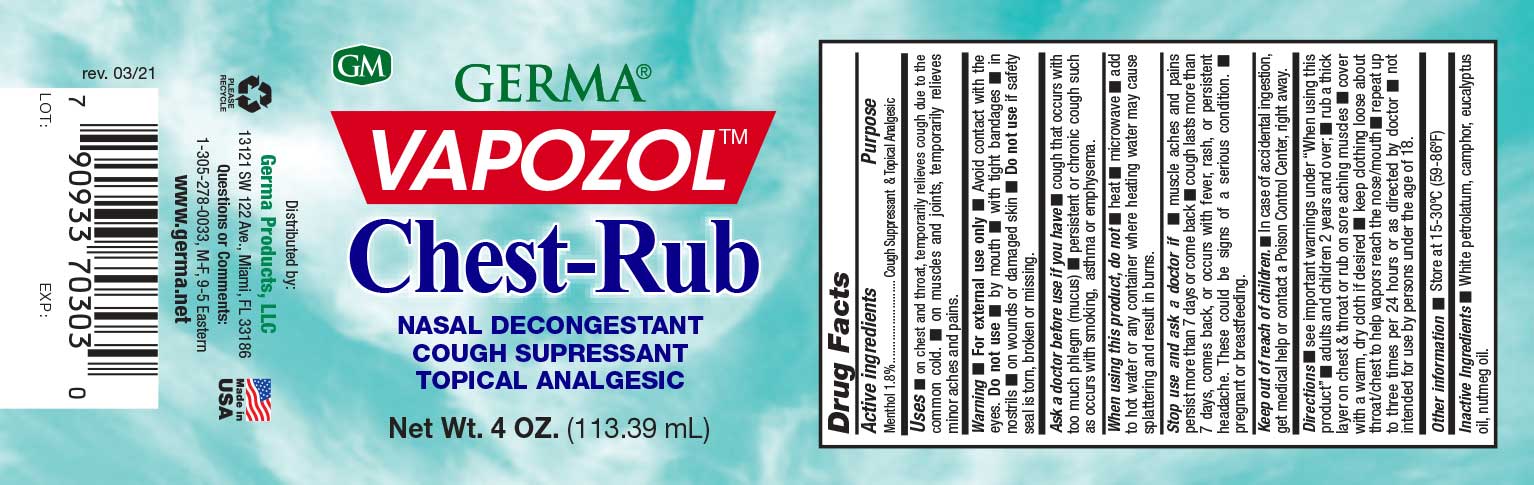 DRUG LABEL: Germa Vapozol
NDC: 73635-5801 | Form: OINTMENT
Manufacturer: Germa Products, LLC
Category: otc | Type: HUMAN OTC DRUG LABEL
Date: 20251010

ACTIVE INGREDIENTS: MENTHOL 18 mg/1 mL
INACTIVE INGREDIENTS: EUCALYPTUS OIL; CAMPHOR (SYNTHETIC); WHITE PETROLATUM; NUTMEG OIL

Vapozol Chest Rub

Active Ingredient

Menthol 1.8%

Uses

Uses • on chest and throat, temporarily relieves cough due to the common cold. • on muscles and joints, temporarily relieves minor aches and pains.

When using this product, do not • heat n microwave • add to hot water or any container where heating water may cause splattering and result in burns.

Purpose

Cough Suppressant & Topical Analgesic

Warnings

For external use only • Avoid contact with the eyes. Do not use • by mouth • with tight bandages • in nostrils • on wounds or damaged skin • Do not use if safety seal is torn, broken or missing.

Warnings

Keep out of reach of children. • In case of accidental ingestion, get medical help or contact a Poison Control Center, right away.

Stop use and ask a doctor if pregnant or breastfeeding.

Stop use and ask a doctor if • muscle aches and pains persist more than 7 days or come back • cough lasts more than 7 days, comes back, or occurs with fever, rash, or persistent headache. These could be signs of a serious condition. • pregnant or breastfeeding.

Ask a doctor before use if you have n cough that occurs with too much phlegm (mucus) n persistent or chronic cough such as occurs with smoking, asthma or emphysema.

Other Information

Store at controlled room temperature 15-30ºC (59-86ºF)

Directions

Directions • see important warnings under “When using this product” • adults and children 2 years and over; • rub a thick layer on chest & throat or rub on sore aching muscles • cover with a warm, dry cloth if desired • keep clothing loose about throat/chest to help vapors reach the nose/mouth • repeat up to three times per 24 hours or as directed by doctor • not intended for use by persons under the age of 18.

Inactive Ingredients

White petrolatum, camphor, eucalyptus oil, nutmeg oil.